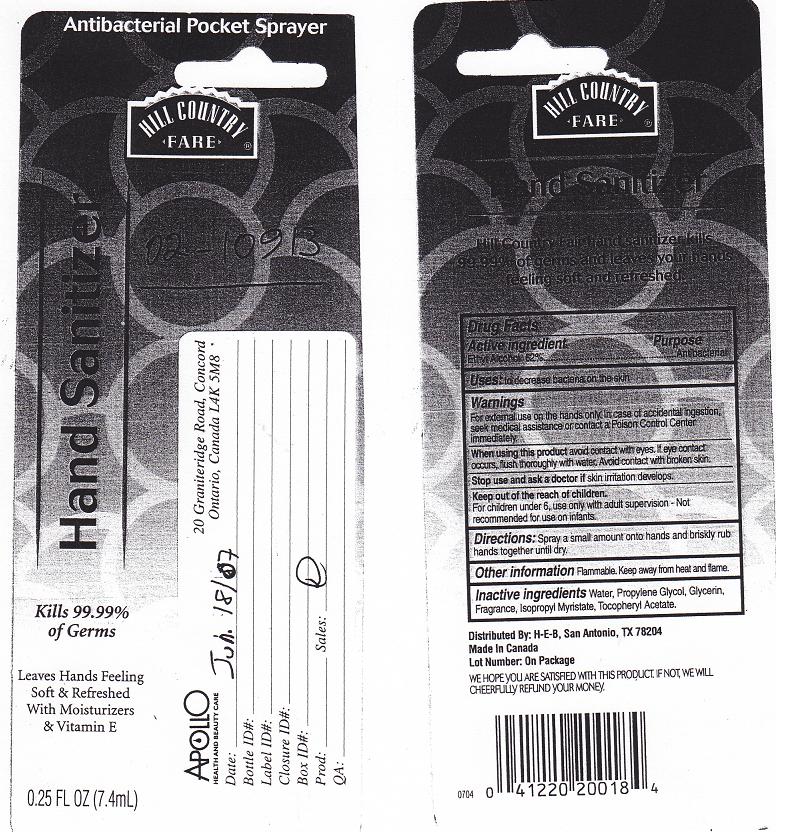 DRUG LABEL: ANTIBACTERIAL
NDC: 37808-235 | Form: LIQUID
Manufacturer: H E B
Category: otc | Type: HUMAN OTC DRUG LABEL
Date: 20110808

ACTIVE INGREDIENTS: ALCOHOL 62 mL/100 mL
INACTIVE INGREDIENTS: WATER; PROPYLENE GLYCOL; GLYCERIN; ISOPROPYL MYRISTATE; .ALPHA.-TOCOPHEROL ACETATE, D-

DRUG FACTS

ACTIVE INGREDIENT

ETHYL ALCOHOL 62%

PURPOSE

ANTIBACTERIAL

USES

TO DECREASE THE BACTERIA ON THE SKIN

WARNINGS

FOR EXTERNAL USE ON THE HANDS ONLY. IN CASE OF ACCIDENTAL INGESTION SEEK MEDICAL ASSISTANCE OR CONTACT A POISON CONTROL CENTER IMMEDIATELY.

WHEN USING THIS PRODUCT

AVOID CONTACT WITH EYES. IF EYE CONTACT OCCURS, FLUSH THOROUGHLY WITH WATER. AVOID CONTACT WITH BROKEN SKIN.

STOP USE AND ASK DOCTOR

IF SKIN IRRITATION DEVELOPS

KEEP OUT OF THE REACH OF CHILDREN

FOR CHILDREN UNDER 6, USE ONLY WITH ADULT SUPERVISION. NOT RECOMMENDED FOR USE ON INFANTS.

DIRECTIONS

SPRAY A SMALL AMOUNT ONTO HANDS AND BRISKLY RUB HANDS TOGETHER UNTIL DRY

OTHER INFORMATION

FLAMMABLE. KEEP AWAY FROM HEAT AND FLAME.

INACTIVE INGREDIENTS

WATER, PROPYLENE GLYCOL, GLYCERIN, FRAGRANCE, ISOPROPYL MYRISTATE, TOCOPHERYL ACETATE.